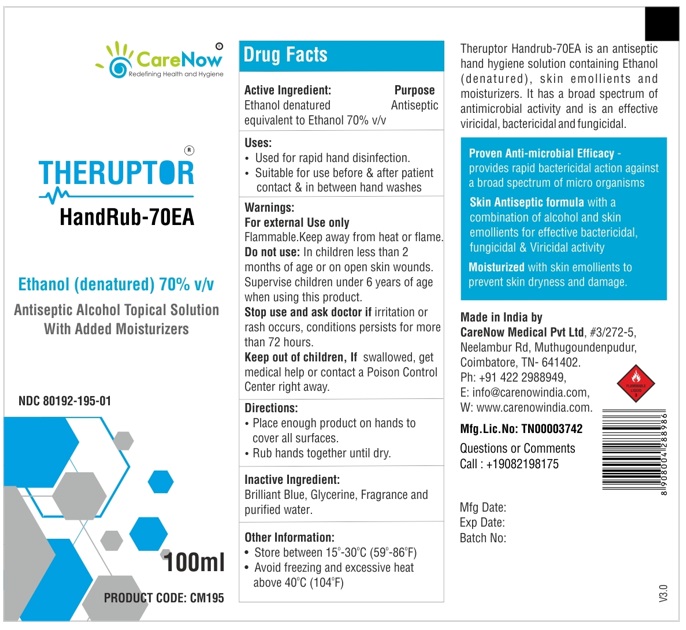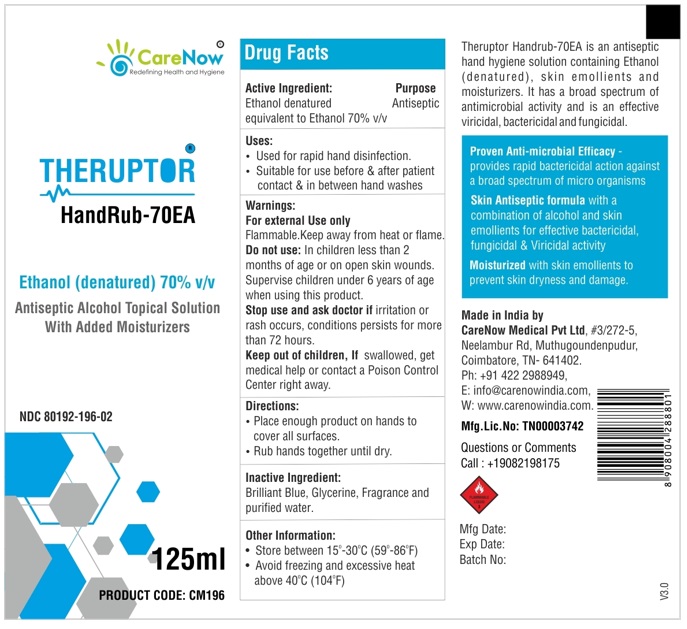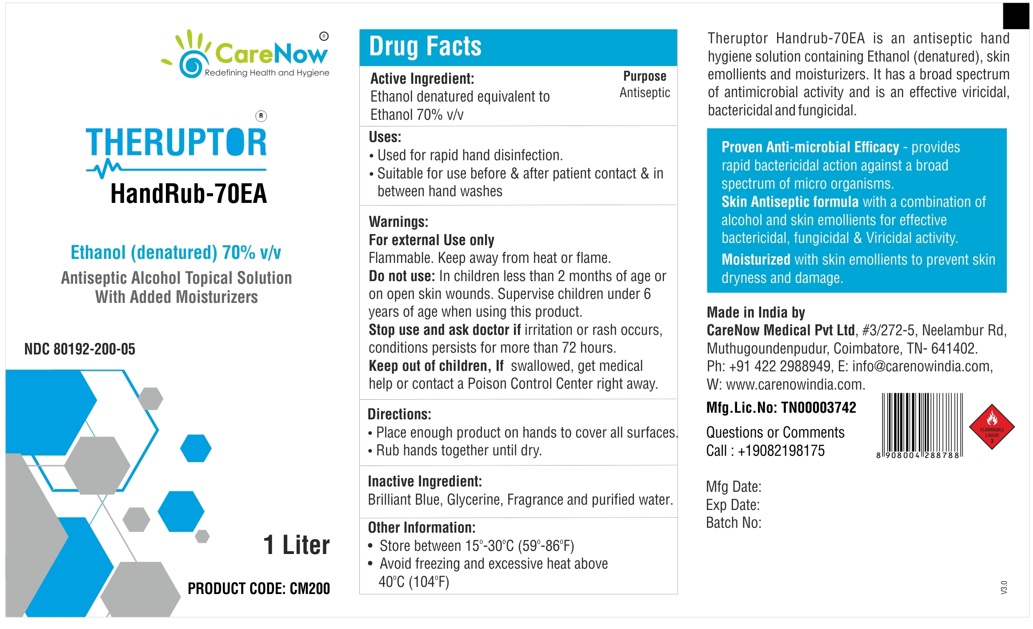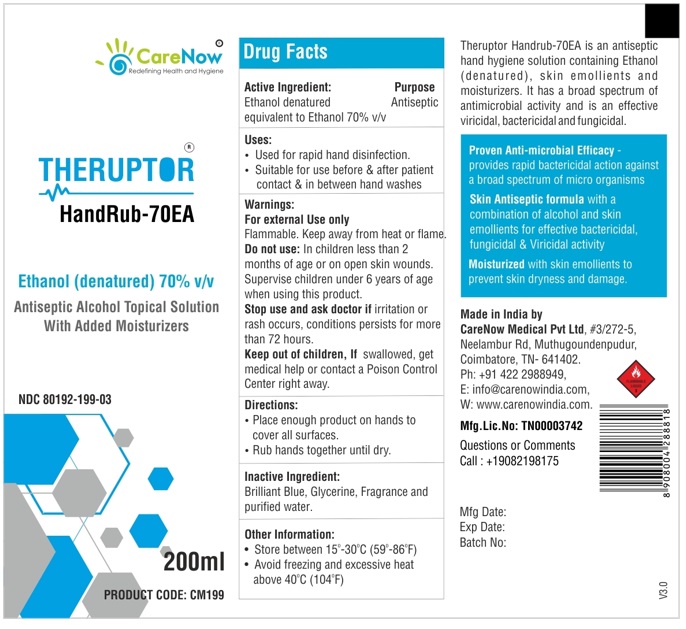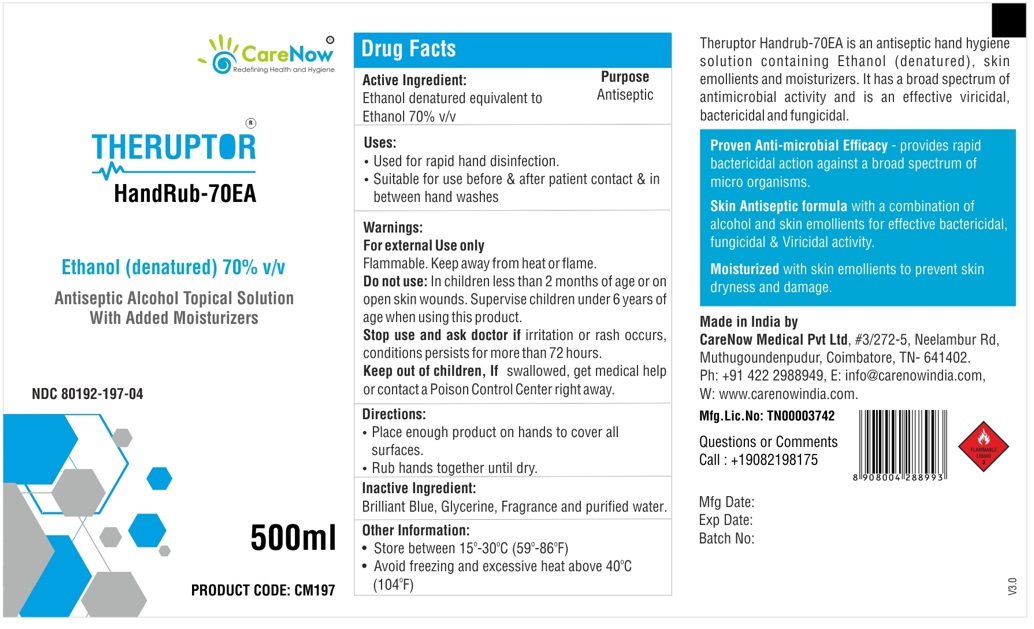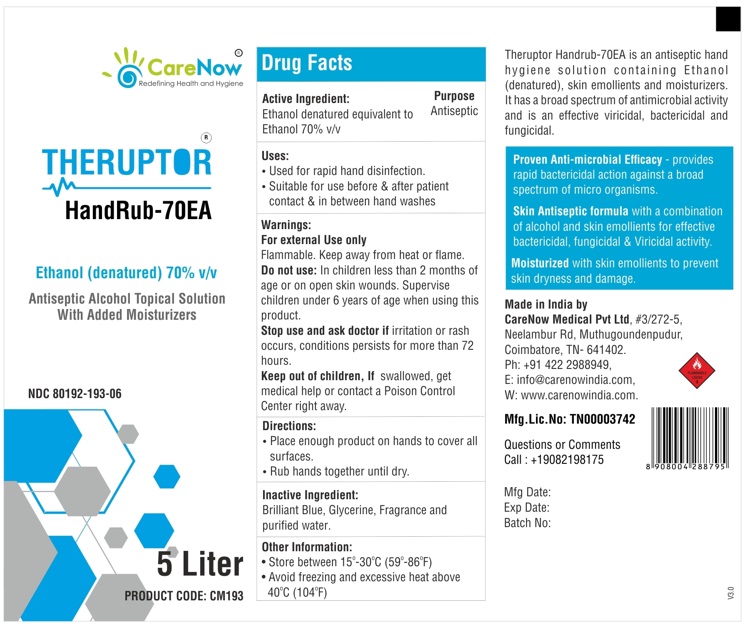 DRUG LABEL: THERUPTOR
NDC: 80192-195 | Form: SOLUTION
Manufacturer: CareNow Medical Pvt Ltd
Category: otc | Type: HUMAN OTC DRUG LABEL
Date: 20220520

ACTIVE INGREDIENTS: ALCOHOL 70 mL/100 mL
INACTIVE INGREDIENTS: FD&C BLUE NO. 1; GLYCERIN; WATER

THERUPTOR®
HandRub-70EA

Ethanol (denatured) 70% v/v
Antiseptic Alcohol Topical Solution With Added Moisturizers

Active Ingredient:
Ethanol denatured equivalent to
Ethanol 70% v/v

Purpose
Antiseptic

Uses:

- Used for rapid hand disinfection.
- Suitable for use before & after patient contact & in between hand washes

Warnings:

For external Use only
Flammable. Keep away from heat or flame.

Do not use: In children less than 2 months of age or on open skin wounds. Supervise children under 6 years of age when using this product.

Stop use and ask doctor if irritation or rash occurs, conditions persists for more than 72 hours.

KEEP OUT OF REACH OF CHILDREN

Keep out of children, If swallowed, get medical help or contact a Poison Control Center right away.

Directions:

- Place enough product on hands to cover all surfaces.
- Rub hands together until dry.

Inactive Ingredient:
Brilliant Blue, Glycerine, Fragrance and purified water.

Other Information:

- Store between 15°-30°C (59°-86°F)
- Avoid freezing and excessive heat above 40°C (104°F)

Theruptor Handrub-70EA is an antiseptic hand hygiene solution containing Ethanol (denatured), skin emollients and moisturizers. It has a broad spectrum of antimicrobial activity and is an effective viricidal, bactericidal and fungicidal.

Proven Anti-microbial Efficacy - provides rapid bactericidal action against a broad spectrum of micro organisms.

Skin Antiseptic formula with a combination of alcohol and skin emollients for effective bactericidal, fungicidal & Viricidal activity.

Moisturized with skin emollients to prevent skin dryness and damage.

Made in India by
CareNow Medical Pvt Ltd, #3/272-5, Neelambur Rd, Muthugoundenpudur, Coimbatore, TN- 641402
Ph: +91 422 2988949, E: info@carenowindia.com, W: www.carenowindia.com

Mfg.Lic.No: TN00003742

Questions or Comments
Call : +19082198175

PRINCIPAL DISPLAY PANEL

NDC 80192-195-01

THERUPTOR®
HandRub-70EA - 100 mL

NDC 80192-196-02

THERUPTOR®
HandRub-70EA - 125 mL

NDC 80192-199-03

THERUPTOR®
HandRub-70EA - 200 mL

NDC 80192-197-04

THERUPTOR®
HandRub-70EA - 500 mL

NDC 80192-200-05

THERUPTOR®
HandRub-70EA - 1 L

NDC 80192-193-06

THERUPTOR®
HandRub-70EA - 5 L